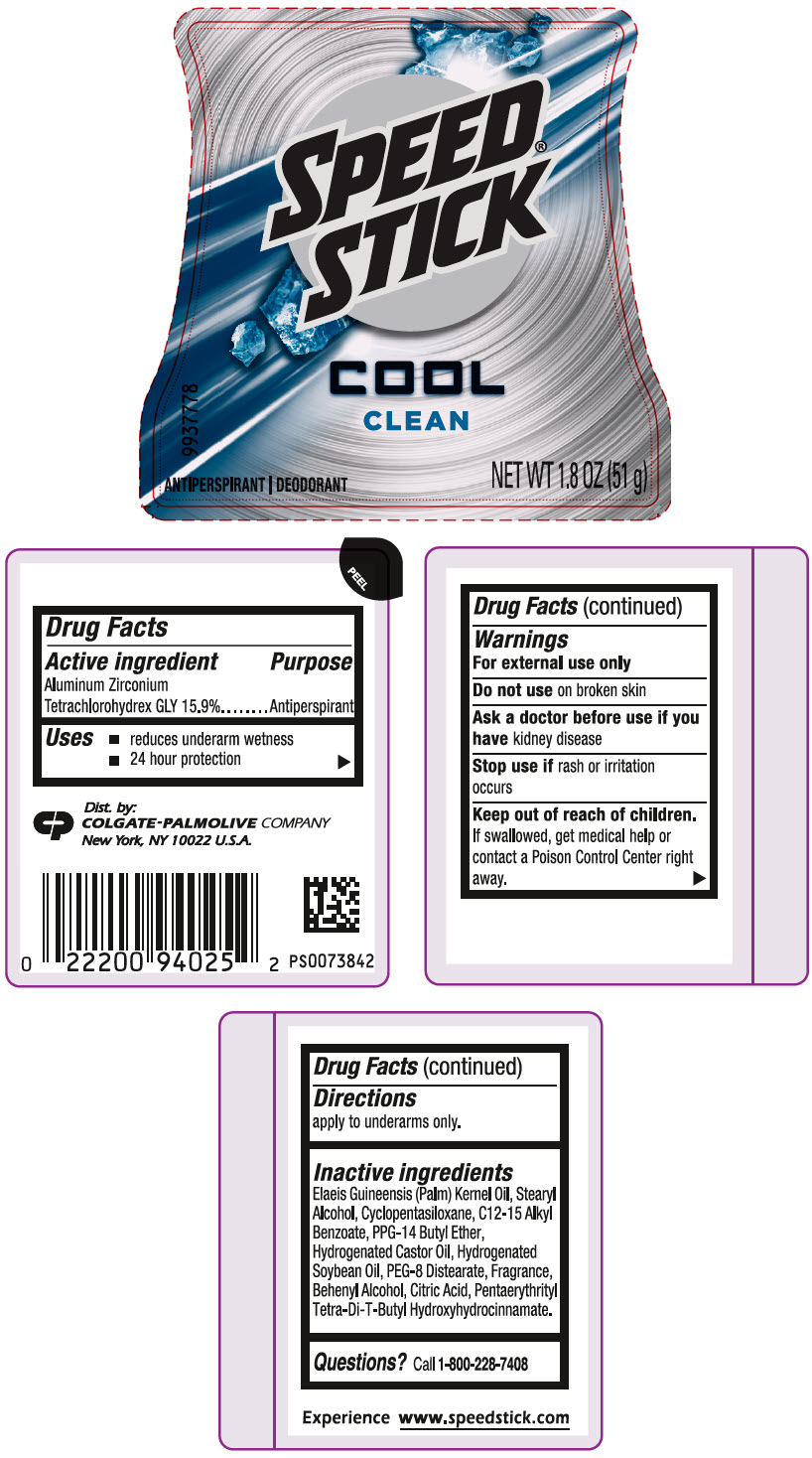 DRUG LABEL: Speed Stick Clean Antiperspirant Deodorant
NDC: 35000-244 | Form: STICK
Manufacturer: Colgate-Palmolive Company
Category: otc | Type: HUMAN OTC DRUG LABEL
Date: 20251219

ACTIVE INGREDIENTS: ALUMINUM ZIRCONIUM TETRACHLOROHYDREX GLY 159 mg/1 g
INACTIVE INGREDIENTS: PALM KERNEL OIL; STEARYL ALCOHOL; CYCLOMETHICONE 5; ALKYL (C12-15) BENZOATE; PPG-14 BUTYL ETHER; HYDROGENATED CASTOR OIL; HYDROGENATED SOYBEAN OIL; PEG-8 DISTEARATE; DOCOSANOL; ANHYDROUS CITRIC ACID; PENTAERYTHRITOL TETRAKIS(3-(3,5-DI-TERT-BUTYL-4-HYDROXYPHENYL)PROPIONATE)

Speed Stick® Clean Antiperspirant Deodorant

Drug Facts

Active ingredient

Aluminum Zirconium Tetrachlorohydrex GLY 15.9%

Purpose

Antiperspirant

Uses

- reduces underarm wetness
- 24 hour protection

Warnings

For external use only

Do not use on broken skin

Ask a doctor before use if you have kidney disease

Stop use if rash or irritation occurs

Keep out of reach of children.

If swallowed, get medical help or contact a Poison Control Center right away.

Directions

apply to underarms only.

Inactive ingredients

Elaeis Guineensis (Palm) Kernel Oil, Stearyl Alcohol, Cyclomethicone, C12-15 Alkyl Benzoate, PPG-14 Butyl Ether, Hydrogenated Castor Oil, Hydrogenated Soybean Oil, PEG-8 Distearate, Fragrance, Behenyl Alcohol, Citric Acid, Pentaerythrityl Tetra-di-t-butyl Hydroxyhydrocinnamate.

Questions?

Call 1-800-228-7408

Dist. by:
COLGATE-PALMOLIVE COMPANY
New York, NY 10022 U.S.A.

PRINCIPAL DISPLAY PANEL - 51 g Container Label

SPEED
STICK®

COOL

CLEAN

9937778

ANTIPERSPIRANT | DEODORANT

NET WT 1.8 OZ (51 g)